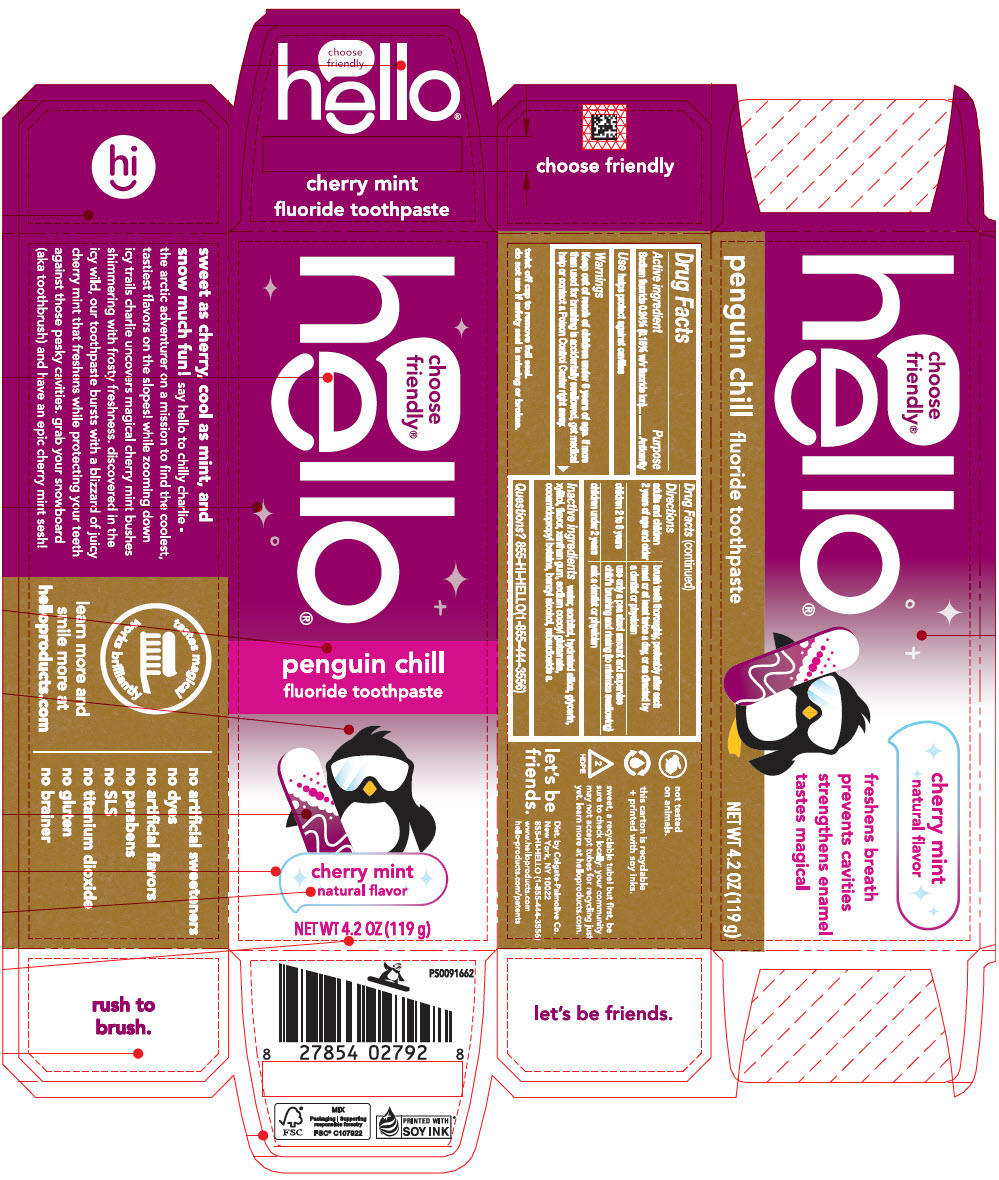 DRUG LABEL: Hello Penguin Chill
NDC: 35000-693 | Form: PASTE, DENTIFRICE
Manufacturer: Colgate-Palmolive Company
Category: otc | Type: HUMAN OTC DRUG LABEL
Date: 20251023

ACTIVE INGREDIENTS: SODIUM FLUORIDE 1.1 mg/1 g
INACTIVE INGREDIENTS: WATER; SORBITOL; HYDRATED SILICA; GLYCERIN; XYLITOL; XANTHAN GUM; SODIUM COCOYL GLUTAMATE; COCAMIDOPROPYL BETAINE; BENZYL ALCOHOL; REBAUDIOSIDE A

Hello® Penguin Chill

Drug Facts

Active ingredient

Sodium fluoride 0.24% (0.15% w/v fluoride ion)

Purpose

Anticavity

Use

helps protect against cavities

Warnings

Keep out of reach of children under 6 years of age. If more than used for brushing is accidentally swallowed, get medical help or contact a Poison Control Center right away.

Directions

adults and children 2 years of age and older | brush teeth thoroughly, preferably after each meal or at least twice a day, or as directed by a dentist or physician
children 2 to 6 years | use only a pea sized amount and supervise child's brushing and rinsing (to minimize swallowing)
children under 2 years | ask a dentist or physician

Inactive ingredients

water, sorbitol, hydrated silica, glycerin, xylitol, flavor, xanthan gum, sodium cocoyl glutamate, cocamidopropyl betaine, benzyl alcohol, rebaudioside a.

Questions?

855-HI-HELLO(1-855-444-3556)

Dist. by Colgate-Palmolive Co.
New York, NY 10022

PRINCIPAL DISPLAY PANEL - 119 g Tube Carton

choose
friendly®
hello®

penguin chill
fluoride toothpaste

cherry mint
natural flavor

NET WT 4.2 OZ (119 g)